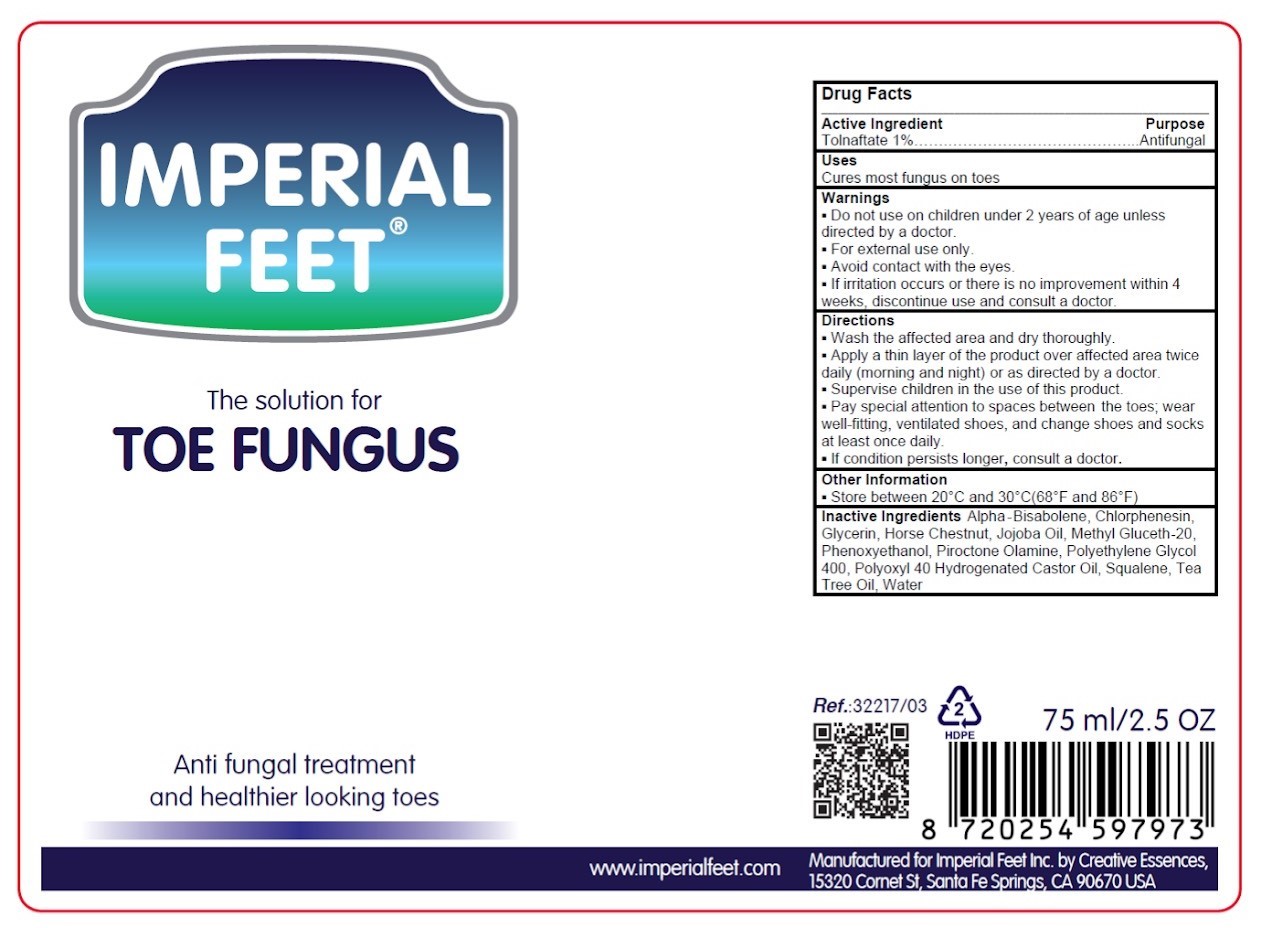 DRUG LABEL: Toe Fungus
NDC: 83837-001 | Form: SOLUTION
Manufacturer: Imperial Feet B.V.
Category: otc | Type: HUMAN OTC DRUG LABEL
Date: 20251017

ACTIVE INGREDIENTS: TOLNAFTATE 1 g/100 mL
INACTIVE INGREDIENTS: SQUALENE; WATER; .ALPHA.-BISABOLENE; PHENOXYETHANOL; METHYL GLUCETH-20; JOJOBA OIL; HORSE CHESTNUT; POLYETHYLENE GLYCOL 400; PIROCTONE OLAMINE; CHLORPHENESIN; POLYOXYL 40 HYDROGENATED CASTOR OIL; GLYCERIN; TEA TREE OIL

Imperial Feet Toe Fungus 83837-001-01

Active ingredient

Tolnaftate

Ask a doctor

If irritation occurs or there is no improvement within 4 weeks, discontinue use and consult a doctor

Purpose

Antifungal

Use

Cures most fungus on toes

Keep out of reach of children

Supervise children in the use of this product.

Stop Use Section

If irritation occurs or there is no improvement within 4 weeks, discontinue use and consult a doctor.

Directions

- Wash the affected area and dry thoroughly.
- Apply a thin layer of the product over affected are twice daily (morning and night) or as directed by a doctor.
- Supervise children in the use of this product.
- Pay special attention to spaces between toes; wear well-fitting, ventilated shoes, and change shoes and socks at least once daily.
- If condition persists longer, consult a doctor.

Warnings

- Do not use on children under 2 years of age unless directed by a doctor.
- For external use only.
- Avoid contact with the eyes.
- If irritation occurs or there is no improvement within 4 weeks, discontinue use and consult a doctor.

Other Information

Store between 20 C and 30 C (68 F and 86 F)

Inactive Ingredients

Alpha-Bisabolene, Chlorphenesin, Glycerin, Horse Chestnut, Jojoba Oil, Methyl Gluceth-20, Phenoxyethanol, Piroctone Olamine, Polyethylene Glycol 400, Polyoxyl 40 Hydrogenated Castor Oil, Squalene, Tea Tree Oil, Water